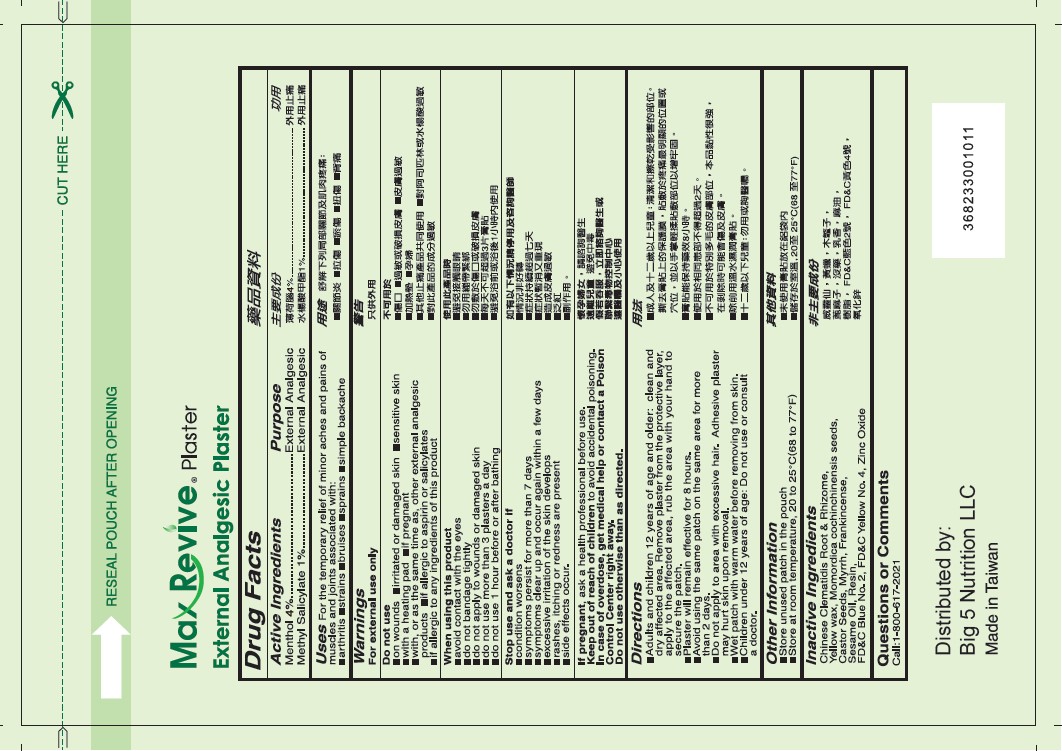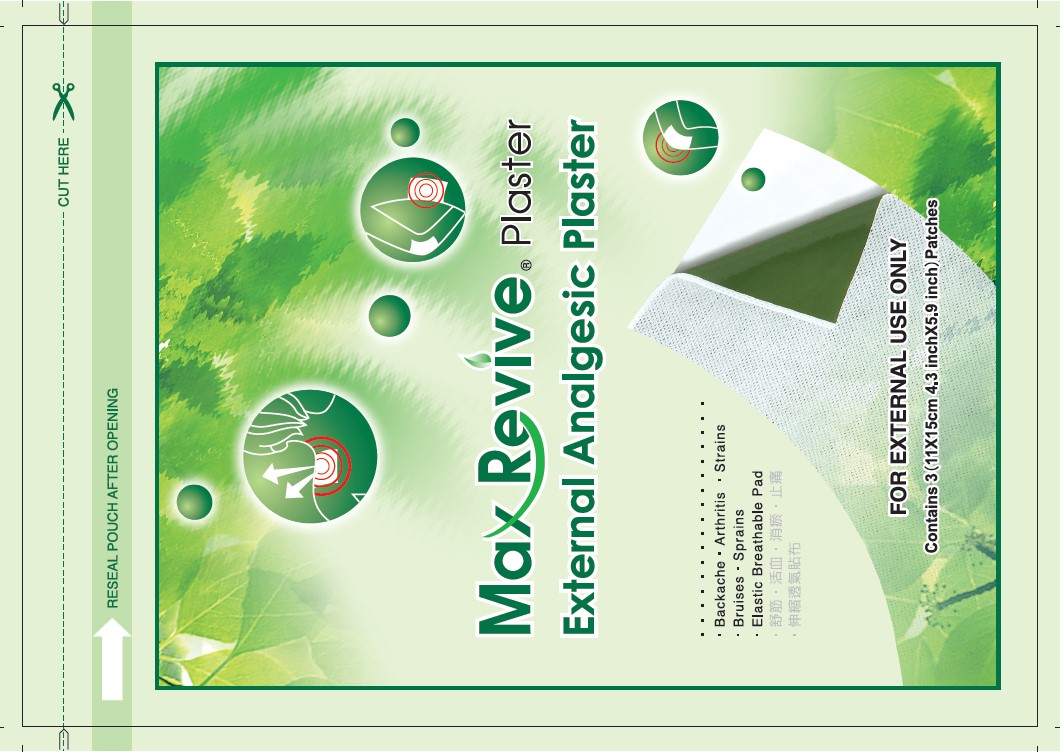 DRUG LABEL: Max Revive Plaster
NDC: 82198-0001 | Form: PATCH
Manufacturer: Big 5 Nutrition LLC
Category: otc | Type: HUMAN OTC DRUG LABEL
Date: 20231120

ACTIVE INGREDIENTS: MENTHOL, UNSPECIFIED FORM 0.04 g/1 g; METHYL SALICYLATE 0.01 g/1 g
INACTIVE INGREDIENTS: MOMORDICA COCHINCHINENSIS SEED; CLEMATIS CHINENSIS ROOT; YELLOW WAX; SESAME OIL; FRANKINCENSE; YELLOW OB; RICINUS COMMUNIS SEED; MYRRH; PINUS MASSONIANA RESIN; FD&C BLUE NO. 2; ZINC OXIDE

MAXREVIVE®PLASTER External Analgesic Prlaster

PURPOSE

Backache, Arthritis, Strains, Bruises, Sprains

Drug Facts

Active Ingredients | Purpose
Menthol 4% | External Analgesic
Methyl Salicylate 1% | External Analgesic

Uses

For the temporary relief of minor aches and pains of
muscles and joints associated with: ■ arthritis ■ strains ■ bruises ■ sprains ■ simple backache

Warnings

For external use only

Do not use

■ on wounds ■ irritated or damaged skin ■ sensitive skin ■ with a heating pad ■ if pregnant ■ with, or as the same time as, other external analgesic P.roducts ■ if allergic to aspirin or salicylates ■ 1f allergic to any ingredients of this product

When using this product

■ avoid contact with the eyes
■ do not bandage tightly
■ do not apply to wounds or damaged skin
■ do not use more than 3 plasters a day
■ do not use 1 hour before or after bathing

Stop use and ask a doctor if

■ condition worsens
■ symptoms persist for more than 7 days
■ symptoms clear up and occur again within a few days
■ excessive irritation of the skin develops
■ rashes, itching or redness are present
■ side effects occur.

PREGNANCY OR BREAST FEEDING

If pregnant. ask a health professional before use.

KEEP OUT OF REACH OF CHILDREN

Keep out of reach of childrento avoid accidental poisoning

OVERDOSAGE

In case of overdose, get medical help or contact a Poison Control Center right away.

Do not use otherwise than as directed.

Directions

■ Adults and children 12 years of age and older: clean and dry affected area. Remove plaster from the protective layer, apply to the affected area, rub the area with your hand to secure the patch.
■ Plaster will remain effective for 8 hours.
■ Avoid using the same patch on the same area for more than 2 days.
■ Do not apply to area with excessive hair. Adhesive plaster may hurt skin upon removal.
■ Wet patch with warm water before removing from skin.
■ Children under 12 years of age: Do not use or consult a doctor.

Other Information

■ Store unused patch in the pouch
■ Store at room temperature, 20 to 25°C(68 to 77°F)

Inactive Ingredients

Chinese Clematidis Root & Rhizome,Yellow wax, Momordica cochinchinensis seeds, Castor Seeds, Myrrh, Frankincense, Sesame Oil, Resin, FD&C Blue No_ 2, FD&C Yellow No. 4, Zinc Oxide

Questions or Comments

Call: 1-800-617-2021